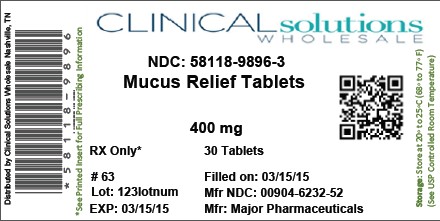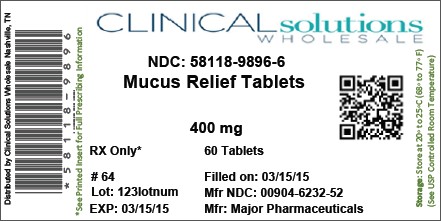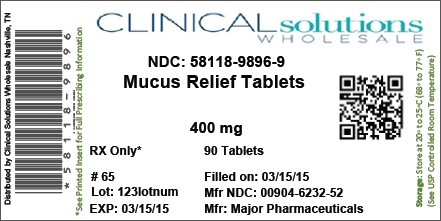 DRUG LABEL: MUCUS RELIEF
NDC: 58118-9896 | Form: TABLET
Manufacturer: Clinical Solutions Wholesale
Category: otc | Type: HUMAN OTC DRUG LABEL
Date: 20131120

ACTIVE INGREDIENTS: GUAIFENESIN 400 mg/1 1
INACTIVE INGREDIENTS: SILICON DIOXIDE; MAGNESIUM STEARATE; MALTODEXTRIN; CELLULOSE, MICROCRYSTALLINE; POVIDONES; SODIUM STARCH GLYCOLATE TYPE A POTATO; STEARIC ACID

Mucus Relief 400mg

ACTIVE INGREDIENT: Each immediate-release tablet contains – Guaifenesin 400 mg

PURPOSE: Expectorant

KEEP OUT OF REACH OF CHILDREN: In case of overdose, get medical help or contact a Poison Control Center right away

INDICATIONS AND USAGE

Helps loosen phlegm (mucus) and thin bronchial secretions to make coughs more productive to rid the bronchial passageway of bothersome mucus.

Ask a doctor before use if you have:

Persistent or chronic cough such as occurs with smoking, asthma, chronic bronchitis, or emphysema.

Cough accompanied by excessive phlegm (mucus)

DOSAGE AND ADMINISTRATION

Adults and children 12 years of age and older, take 1 tablet every 4 hours with a full glass of water while symptoms persist. Do not exceed 6 doses in 24 hours.

Children under 12 years of age do not use.

INACTIVE INGREDIENT

Colloidal Silicon Dioxide, Magnesium Stearate, Maltodextrin, Microcrystalline Cellulose, Povidone, Silicon Dioxide, Sodium Starch Glycolate, Stearic Acid